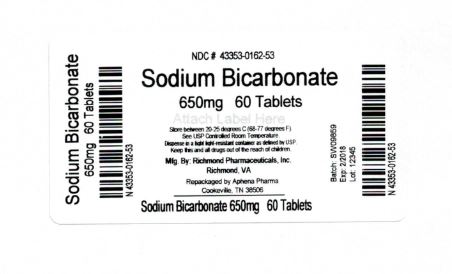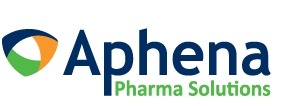 DRUG LABEL: SODIUM BICARBONATE
NDC: 43353-162 | Form: TABLET
Manufacturer: Aphena Pharma Solutions - Tennessee, LLC
Category: otc | Type: HUMAN OTC DRUG LABEL
Date: 20171213

ACTIVE INGREDIENTS: SODIUM BICARBONATE 650 mg/1 1
INACTIVE INGREDIENTS: CROSCARMELLOSE SODIUM; MICROCRYSTALLINE CELLULOSE; STEARIC ACID

SODIUM BICARBONATE 10 gr (650 mg)

Drug Facts

Active Ingredient (in each tablet)

Sodium bicarbonate 10 gr (650 mg)

PURPOSE

Antacid

Indications:

Relieves:

- acid indigestion
- heartburn
- sour stomach
- upset stomach associated with these symptoms

Warnings

Ask a doctor or pharmacist

- if you are on a sodium-restricted diet.
- if you are taking a prescription drug. Antacids may interact with certain prescription drugs.
- if symptons last more than 2 weeks

PREGNANCY OR BREAST FEEDING

As with any drug, if you are pregnant or nursing a baby, seek advise of a health professional before using this product.

Directions:

- Adults 60years of age and over - 1-2 tablets every 4 hours. Not more than 12 tablets in 24 hours
- Adults under 60 years- 1-4 tablets every4 hours. Not more than 24 tablets in 24 hours
- Dissolve tabelt completely in water before drinking.
- DO NOT EXCEED RECOMMENDED DOSE. Not recommended for children.

Other Information:

- each tablet contains: sodium 178 mg
- store at room temperature 15°- 30°C (59°- 86°F).

KEEP OUT OF REACH OF CHILDREN

KEEP THIS AND ALL DRUGS OUT OF THE REACH OF CHILDREN.

OVERDOSAGE

In case of accidental overdose, seek professional assistance or contact a poison control center immediately.

INACTIVE INGREDIENT

croscarmellose sodium, microcrystalline cellulose, stearic acid

Questions or Comments

TAMPER EVIDENT: DO NOT USE IF IMPRINTED SAFETY SEAL UNDER CAP IS BROKEN OR MISSING

call 804-270-4498, 8.30 am-4.30 pm ET, Monday - Friday

Repackaging Information

Please reference the How Supplied section listed above for a description of individual tablets. This drug product has been received by Aphena Pharma - TN in a manufacturer or distributor packaged configuration and repackaged in full compliance with all applicable cGMP regulations. The package configurations available from Aphena are listed below:

Count | 650 mg
60 | 43353-162-53
90 | 43353-162-60
120 | 43353-162-70
180 | 43353-162-80
200 | 43353-162-85
360 | 43353-162-94

Store between 20°-25°C (68°-77°F). See USP Controlled Room Temperature. Dispense in a tight light-resistant container as defined by USP. Keep this and all drugs out of the reach of children.

Repackaged by:
Cookeville, TN 38506
20171213JH

PRINCIPAL DISPLAY PANEL - 650 mg

NDC 43353-162 - Sodium Bicarbonate 650 mg - Rx Only